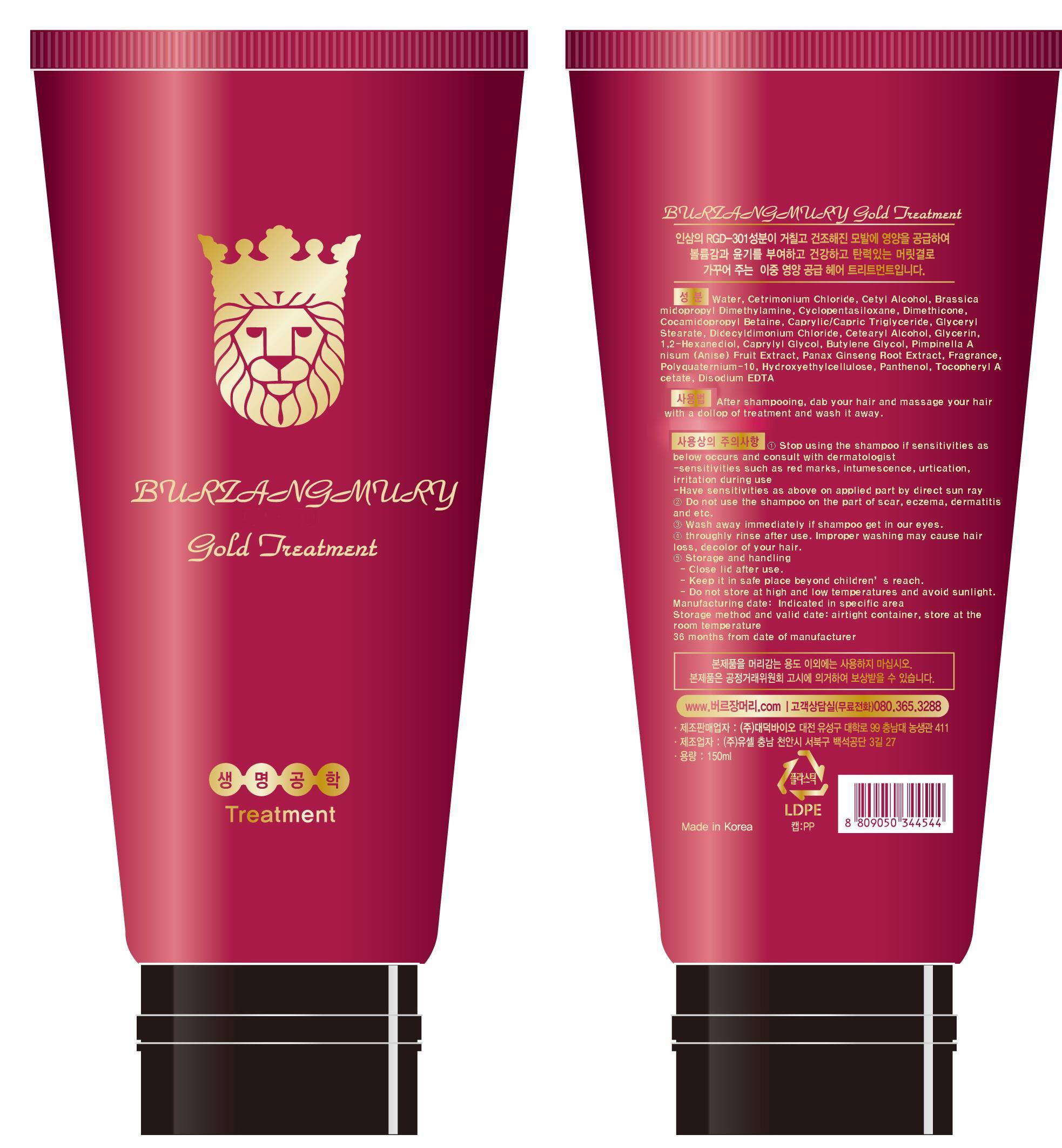 DRUG LABEL: BURZANGMURY GOLD TREATMENT
NDC: 58906-2001 | Form: LIQUID
Manufacturer: Dae Deok bio Inc 
Category: otc | Type: HUMAN OTC DRUG LABEL
Date: 20130816

ACTIVE INGREDIENTS: GLYCERIN 0.01 g/1 mL
INACTIVE INGREDIENTS: WATER; CETRIMONIUM CHLORIDE; CYCLOMETHICONE 5; DIMETHICONE

Drug Facts

ACTIVE INGREDIENT

glycerin

INACTIVE INGREDIENT

Water, Cetrimonium Chloride, cetyl alcohol, cyclopentasiloxane, dimethicone, cocamidoproplyl Betaine, caprlic/capric triglyceride, glyceryl stearate,Dicetyldimonium Chloride, Cetearyl alcohol, glycerin, 1,2-hexandiol, caprylyl Glycol, butylene glycol, ÀÌ´Ð½º¿¸ÅÃßÃâ¹°, ginseng extract, perfume, polyquaternium-10, Hydroxyethylcellulose, panthenol, tocopheryl acetate, disodium EDTA

PURPOSE

hair growth, loss prevention

keep out of reach of the children

INDICATIONS AND USAGE

After shampooing, dab your hair and massage your hair with a dollop of treatment and wash it away

WARNINGS

- Stop using the treatment if sensitivities as below occurs and consult with dermatologist
- sensitivities such as red marks, intumescence, urtication, irritation during use
-Have sensitivities as above on applied part by direct sun ray
- Do not use the shampoo on the part of scar, eczema, dermatitis and etc.
- Wash away immediately if shampoo get in our eyes.
- throughly rinse after use. Improper washing may cause hair loss, decolor of your hair.
- Storage and handling
- Close lid after use.
- Do not store at high and low temperatures and avoid sunlight.

DOSAGE AND ADMINISTRATION

for external use only